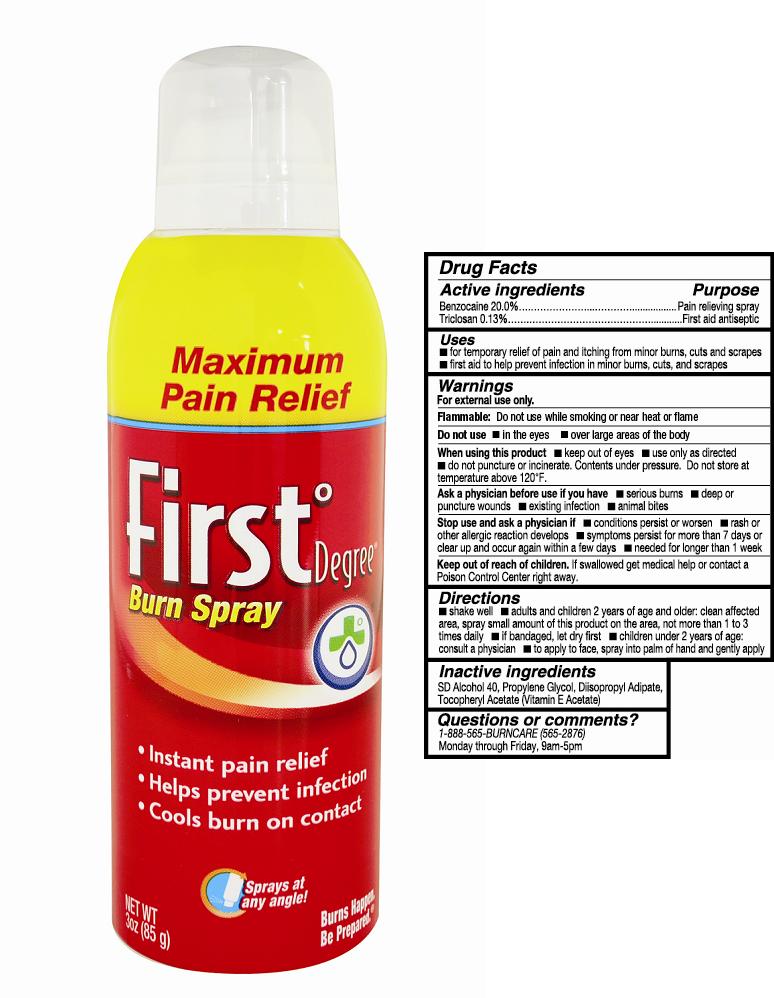 DRUG LABEL: First Degree Burn
NDC: 24330-111 | Form: SPRAY
Manufacturer: The Akshay Wellness Group, Inc.
Category: otc | Type: HUMAN OTC DRUG LABEL
Date: 20130725

ACTIVE INGREDIENTS: BENZOCAINE 200 mg/1 mL; TRICLOSAN 1.3 mg/1 mL
INACTIVE INGREDIENTS: ISOPROPYL ALCOHOL; PROPYLENE GLYCOL; .ALPHA.-TOCOPHEROL ACETATE; DIISOPROPYL ADIPATE

First°Degree® Burn Spray

Active ingredients

Benzocaine 20.0%

Triclosan 0.13%

Purpose

Pain relieving spray

First aid antiseptic

Uses

- for temporary relief of pain and itching from minor burns, cuts and scrapes
- first aid to help prevent infection in minor burns, cuts and scrapes

Warnings

For external use only.

Flammable: Do not use while smoking or near heat or flame.

Do not use

- in the eyes
- over large areas of the body

When using this product

- keep out of eyes
- use only as directed
- do not puncture or incinerate. Contents under pressure. Do not store at
  temperature above 120°F.

Ask a Physician before use if you have

- serious burns
- deep or puncture wounds
- existing infection
- animal bites

Stop use and ask a physician if

- conditions persist or worsen
- rash or other allergic reaction develops
- symptoms persist for more than 7 days or clear up and occur again within a few days
- needed for longer than 1 week

Keep out of reach of children.

If swallowed get medical help or contact a Poison Control Center right away.

Directions

- shake well
- adults and children 2 years of age and older: clean affected area, spray small amount of this product on the area, not more than 1 to 3 times daily
- if bandaged, let dry first
- children under 2 years of age: consult a physician
- to apply to face, spray into palm of hand and gently apply

Inactive ingredients

SD Alcohol 40, Propylene Glycol, Disopropyl Adipate, Tocopheryl Acetate (Vitamin E Acetate)

Questions or comments?

1-888-565-BURNCARE (565-2876)
Monday through Friday, 9am-5pm

Principal Display Panel

Maximum Pain Relief

First°Degree® Burn Spray

- instant pain relief
- helps prevent infection
- cools burn on contact

Sprays at an angle!

Burns Happen. Be Prepared.™

Net Wt. 3 oz (85 g)

Drug Facts Panel

Bottle Label